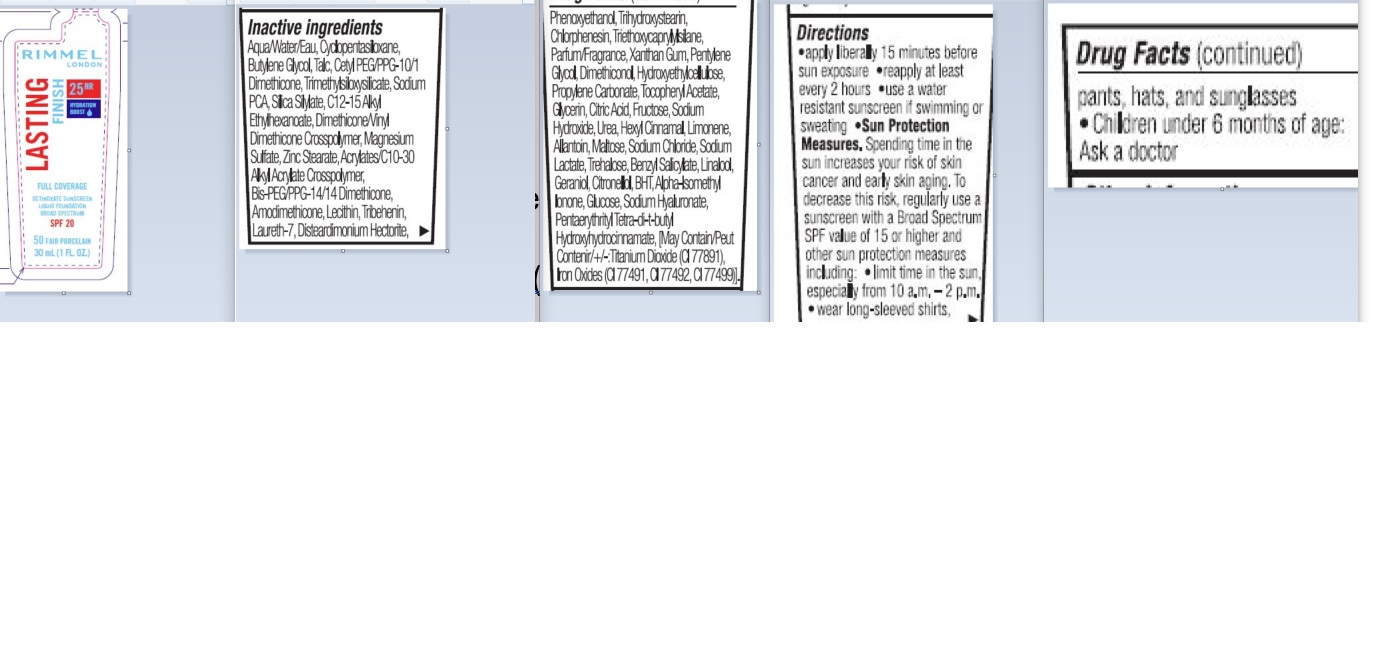 DRUG LABEL: Rimmel London Lasting Finish 25 HR Foundation SPF 20
NDC: 76485-1114 | Form: CREAM
Manufacturer: Rimmel
Category: otc | Type: HUMAN OTC DRUG LABEL
Date: 20241119

ACTIVE INGREDIENTS: OCTINOXATE 2.5 g/100 mL
INACTIVE INGREDIENTS: WATER

Rimmel London Lasting Finish 25 Hr Foundation SPF 20

ACTIVE INGREDIENT

Octinoxate 2.5%

Purpose

Sunscreen

Inactive ingredients

Water, Cyclopentasiloxane, Butylene Glucol, Talc, Cetyl PEG/PPG-10/1 Dimethicone, Trimethylsiloxysilicate, Sodium PCA, Silica Silylate, C12-15 Alkyl Ethylhexanoate, Dimethicone/vinyl Dimethicone Crosspolymer, Magnesium Sulfate, Zinc Stearate, Acrylates/C10-30 Alkyl Acrylate Crosspolymer, Bis-PEG/PPG- 14/14 Dimethicone, Amodimethicone, Lecithin, Tribehenin, Laureth-7, Disteardimonium Hectorite, Phenoxyethanol, Trihydroxystearin, Chlorphenesin, Triethoxycaprylysilance, Parfum.Fragrance, Xanthan Gum, Pentylene Glycol, Dimethiconol, Hydroxyethyleclulose, Propylene Carbonate, Tocopheryl Acetate, Glycerin, Citric Acid, Fructose, Sodium Hydroxide, Urea, Hexyl Cinnamal, Limonene , Allantoin, Maltose, SOdium Chloride, Sodium Lactate, Trehalose, Benzyl Salicylate, Linalool, Geraniol, BHT, Alpha-Isomethyl Lonone, GLucose, Sodium Hyaluraonate, Penaerythrityl Tetra-di-t-butyl Hydroxyhydrocinnamate, [May Contain/Peut Contenir/+-: Titanium Dioxide (CI 77891), Iron Oxides (CI 77491, CI 77492, CI 77499)].

INDICATIONS AND USAGE

- helps prevent sunburn
- If used as directed with other sun protection measures (see Directions), decreases the risk of skin cancer and early skin aging caused by the sun.

Warnings

For external use only.

Do not use

- on damaged or broken skin.

When using this product

- keep out of eyes. Rinse with water to remove.

Stop use and ask a doctor if

- rash occurs.

Keep out of reach of children. If swallowed, get medical help or contact a Poison Control Center right away.

Directions

- apply liberally 15 minutes before sun exposure
- reapply at leaset every 2 hours
- use a water resistant sunscreen if swimming or sweating.

Keep our of reach of children

- Children under 6 months of age: Ask a doctor

Sun Protection Measures

- spending time in the sun increases your risk of skin cancer and early skin aging. To decrease this risk, regulariy use a sunscreen with a Broad Spectrum SPF value of 15 or highter and other sun protection measures including:
- limit time in the sun espiecally from 10 a.m. - 2p.m.
- wear long sleaves, shirts, protect the product in this container from excessive heat and direct sun.